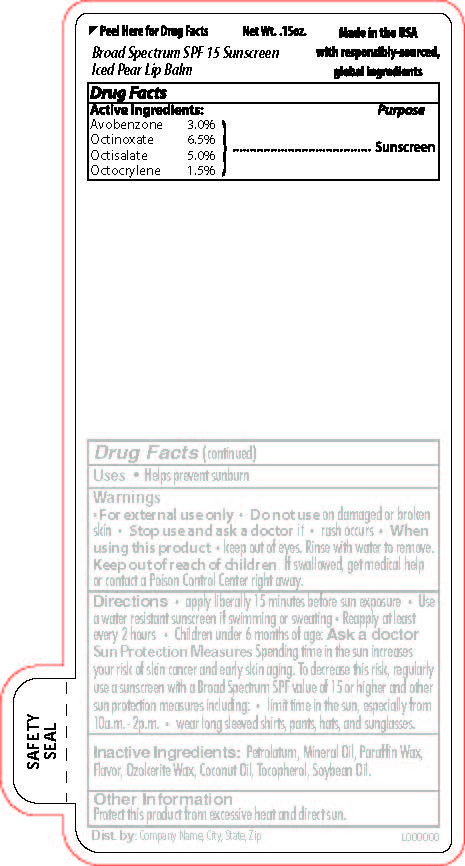 DRUG LABEL: Broad Spectrum SPF 15 Sunscreen Iced Pear Lip Balm
NDC: 65692-0570 | Form: STICK
Manufacturer: Raining Rose
Category: otc | Type: HUMAN OTC DRUG LABEL
Date: 20231026

ACTIVE INGREDIENTS: AVOBENZONE 0.13 g/4.25 g; OCTINOXATE 0.28 g/4.25 g; OCTOCRYLENE 0.06 g/4.25 g; OCTISALATE 0.21 g/4.25 g
INACTIVE INGREDIENTS: WHITE PETROLATUM; PARAFFIN; SOYBEAN OIL; CERESIN; COCONUT OIL; MINERAL OIL; TOCOPHEROL

Broad Spectrum SPF 15 Sunscreen Iced Pear Lip Balm

Active Ingredients:

Avobenzone 3.0%

Octinoxate 6.5%

Octisalate 5.0%

Octocrylene 1.5%

Purpose

Sunscreen

Warnings

For external use only.

Do not use on damaged or broken skin

Stop use and ask doctor if rash occurs

When using this product keep out of eyes. Rinse with water to remove.

Keep out of reach of children. If swallowed, get medical help or contact a Poison Control Center right away.

ROUTE, METHOD AND FREQUENCY OF ADMINISTRATION

Directions: Apply liberally 15 mintues before sun exposure. Use a water resistant sunscreen if swimming or sweating. Reapply at least every 2 hours. Children under 6 months of age: Ask a doctor. Sun Protection Measures Spending time in the sun increases
your risk of skin cancer and early skin aging. To decrease this risk, regularly
use a sunscreen with a Broad Spectrum SPF value of 15 or higher and other
sun protection measures including: • limit time in the sun, especially from
10a.m. - 2p.m. • wear long sleeved shirts, pants, hats, and sunglasses.

Inactive Ingredients: Petrolatum, Mineral Oil, Paraffin Wax,
Flavor, Ozokerite Wax, Coconut Oil, Tocopherol, Soybean Oil.

DOSAGE AND ADMINISTRATION

Apply liberally 15 minutes before sun exposure

INDICATIONS AND USAGE

Helps prevent sunburn